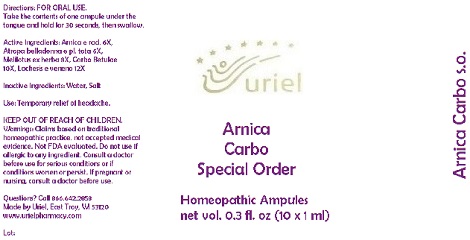 DRUG LABEL: Arnica Carbo Special Order
NDC: 48951-1231 | Form: LIQUID
Manufacturer: Uriel Pharmacy Inc.
Category: homeopathic | Type: HUMAN OTC DRUG LABEL
Date: 20191127

ACTIVE INGREDIENTS: ARNICA MONTANA ROOT 6 [hp_X]/1 mL; ATROPA BELLADONNA 6 [hp_X]/1 mL; MELILOTUS INDICUS SEED 8 [hp_X]/1 mL; ACTIVATED CHARCOAL 10 [hp_X]/1 mL; LACHESIS MUTA VENOM 12 [hp_X]/1 mL
INACTIVE INGREDIENTS: WATER; SODIUM CHLORIDE

Arnica Carbo Special Order

INDICATIONS AND USAGE

Directions: FOR ORAL USE.

DOSAGE AND ADMINISTRATION

Take the contents of one ampule under the tongue and hold for 30 seconds, then swallow.

ACTIVE INGREDIENT

Active Ingredients: Arnica e rad. 6X, Atropa belladonna e pl. tota 6X, Melilotus ex herba 8X, Carbo Betulae 10X, Lachesis e veneno 12X

Inactive Ingredients: Water, Salt

PURPOSE

Use: Temporary relief of headache.

KEEP OUT OF REACH OF CHILDREN.

WARNINGS

Warnings: Claims based on traditional homeopathic practice, not accepted medical evidence. Not FDA evaluated. Do not use if allergic to any ingredient. Consult a doctor before use for serious conditions or if conditions worsen or persist. If pregnant or nursing, consult a doctor before use.

QUESTIONS

Questions? Call 866.642.2858 Made by Uriel, East Troy, WI 53120 www.urielpharmacy.com